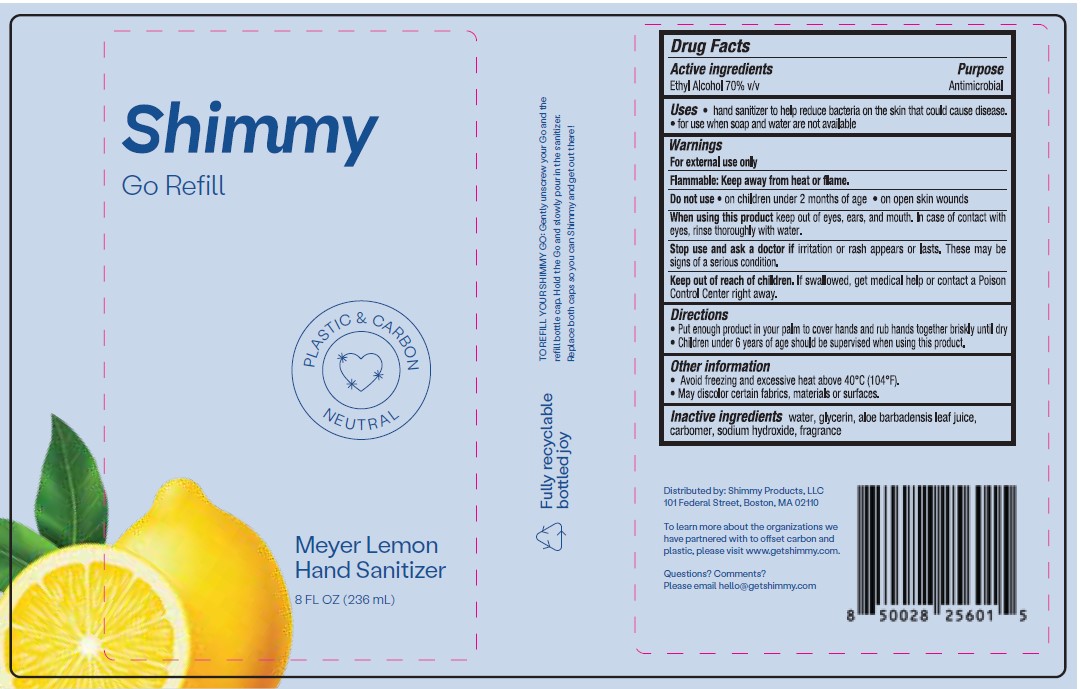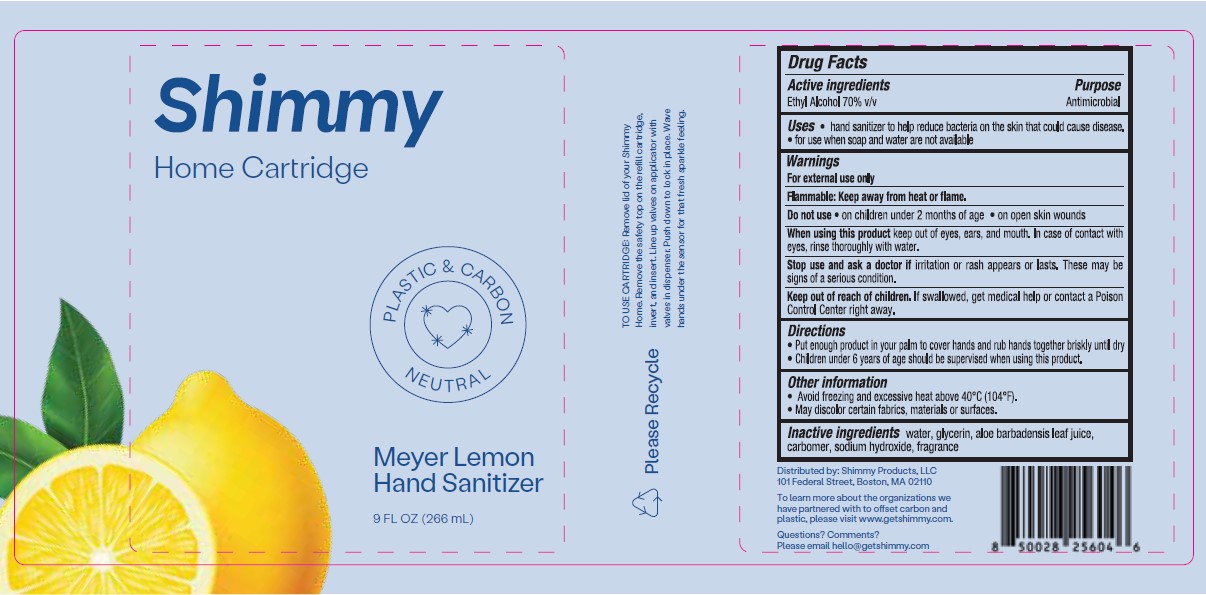 DRUG LABEL: Shimmy Meyer Lemon Hand Sanitizer
NDC: 81755-003 | Form: SPRAY
Manufacturer: Shimmy Products LLC
Category: otc | Type: HUMAN OTC DRUG LABEL
Date: 20240725

ACTIVE INGREDIENTS: ALCOHOL 70 mg/100 mL
INACTIVE INGREDIENTS: SODIUM HYDROXIDE; GLYCERIN; ALOE VERA LEAF; WATER; CARBOMER HOMOPOLYMER TYPE C

SHIMMY MEYER LEMON HAND SANITIZER

Active Ingredients

Ethyl Alcohol 70% v/v

Purpose

Antimicrobial

Uses

- hand sanitizer to help reduce bacteria on the skin that could cause disease.
- for use when soap and water are not available

Warnings

For external use only.

Flammable. Keep away from heat or flame.

Do not use

- on children less than 2 months of age
- on open skin wounds

When using this product

- keep out of eyes, ears, and mouth. In case of contact with eyes, rinse eyes thoroughly with water.

Stop use and ask a doctor

if irritation or rash appears or lasts. These may be signs of a serious condition.

Keep out of reach of children.

If swallowed, get medical help or contact a Poison Control Center right away.

Directions

- Put enough product in your palm to cover your hands and rub hands together briskly until dry
- Children under 6 years of age should be supervised when using this product.

Other information

- Avoid freezing and excessive heat above 40ºC (104ºF).
- May discolor certain fabrics, materials or surfaces.

Inactive ingredients

water, glycerin, aloe barbadensis leaf juice, carbomer, sodium hydroxide, fragrance

Package Label - Principal Display Panel

SHIMMY MEYER LEMON HAND SANITIZER

8 fl oz (236 mL)

NDC: 81755-003-92

SHIMMY MEYER LEMON HAND SANITIZER

9 fl oz (266 mL)

NDC: 81755-003-93